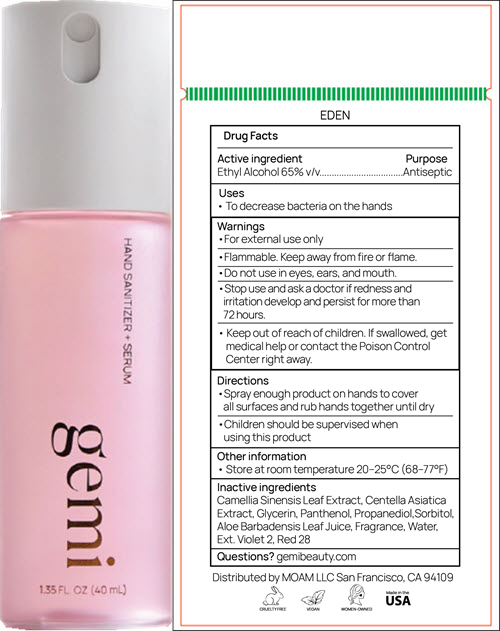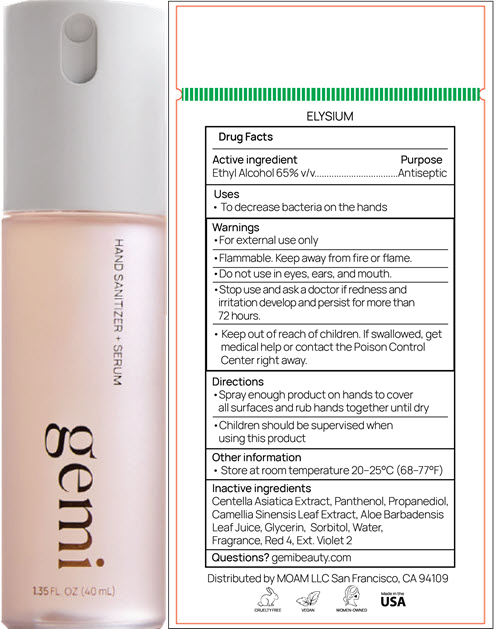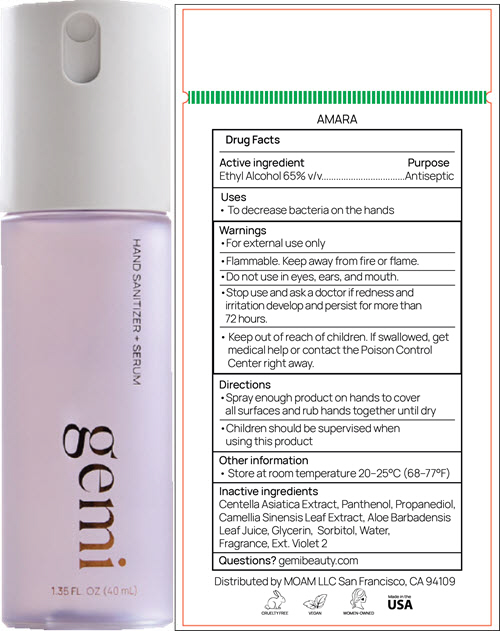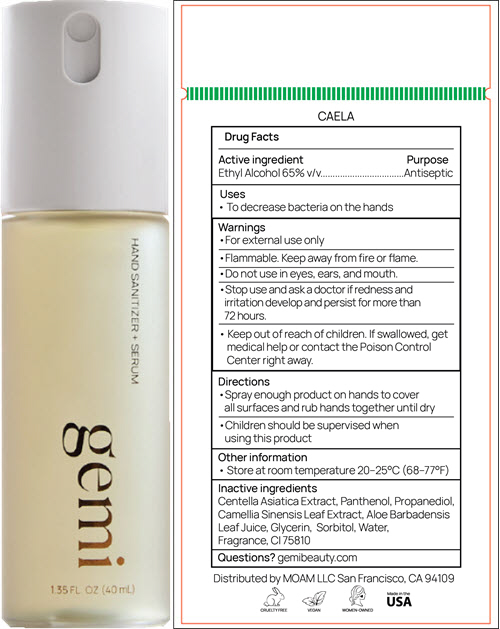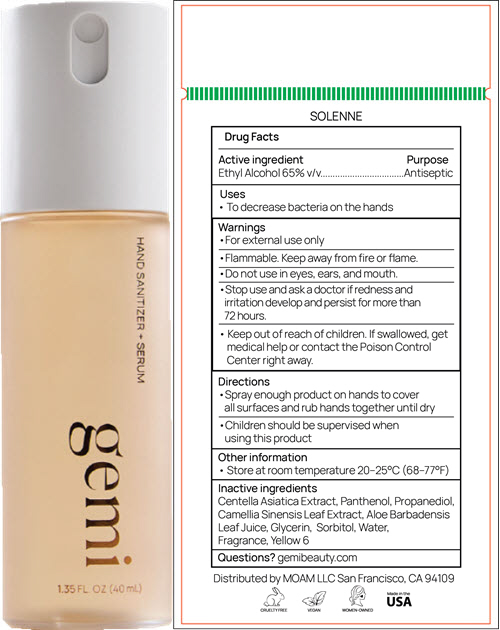 DRUG LABEL: Hand Sanitizer plus Serum
NDC: 85975-101 | Form: SPRAY
Manufacturer: Moam LLC
Category: otc | Type: HUMAN OTC DRUG LABEL
Date: 20250818

ACTIVE INGREDIENTS: Alcohol 26 mL/40 mL
INACTIVE INGREDIENTS: Water; Glycerin; Sorbitol; Propanediol; ALOE VERA LEAF JUICE; Panthenol; GREEN TEA LEAF; EXT. D&C VIOLET NO. 2; D&C RED NO. 28; CENTELLA ASIATICA TRITERPENOIDS

Hand Sanitizer + Serum

Drug Facts

Active ingredient

Ethyl Alcohol 65% v/v

Purpose

Antiseptic

Uses

- To decrease bacteria on the hands

Warnings

- For external use only

WHEN USING

- Flammable. Keep away from fire or flame.

- Do not use in eyes, ears, and mouth.

- Stop use and ask a doctor if redness and irritation develop and persist for more than 72 hours.

- Keep out of reach of children. If swallowed, get medical help or contact the Poison Control Center right away.

Directions

- Spray enough product on hands to cover all surfaces and rub hands together until dry
- Children should be supervised when using this product

Other information

- Store at room temperature 20–25°C (68–77°F)

Inactive ingredients

Camellia Sinensis Leaf Extract, Centella Asiatica Extract, Glycerin, Panthenol, Propanediol,Sorbitol, Aloe Barbadensis Leaf Juice, Fragrance, Water, Ext. Violet 2, Red 28

Inactive ingredients

Centella Asiatica Extract, Panthenol, Propanediol, Camellia Sinensis Leaf Extract, Aloe Barbadensis Leaf Juice, Glycerin, Sorbitol, Water, Fragrance, Red 4, Ext. Violet 2

Inactive ingredients

Centella Asiatica Extract, Panthenol, Propanediol, Camellia Sinensis Leaf Extract, Aloe Barbadensis Leaf Juice, Glycerin, Sorbitol, Water, Fragrance, Ext. Violet 2

Inactive ingredients

Centella Asiatica Extract, Panthenol, Propanediol, Camellia Sinensis Leaf Extract, Aloe Barbadensis Leaf Juice, Glycerin, Sorbitol, Water, Fragrance, Yellow 6

Inactive ingredients

Centella Asiatica Extract, Panthenol, Propanediol, Camellia Sinensis Leaf Extract, Aloe Barbadensis Leaf Juice, Glycerin, Sorbitol, Water, Fragrance, CI 75810

Questions?

gemibeauty.com

Distributed by MOAM LLC San Francisco, CA 94109

PRINCIPAL DISPLAY PANEL - 40 mL Bottle Label - EDEN

HAND SANITIZER + SERUM

gemi

1.35 FL OZ (40 mL)

PRINCIPAL DISPLAY PANEL - 40 mL Bottle Label - ELYSIUM

HAND SANITIZER + SERUM

gemi

1.35 FL OZ (40 mL)

PRINCIPAL DISPLAY PANEL - 40 mL Bottle Label - AMARA

HAND SANITIZER + SERUM

gemi

1.35 FL OZ (40 mL)

PRINCIPAL DISPLAY PANEL - 40 mL Bottle Label - CAELA

HAND SANITIZER + SERUM

gemi

1.35 FL OZ (40 mL)

PRINCIPAL DISPLAY PANEL - 40 mL Bottle Label - SOLENNE

HAND SANITIZER + SERUM

gemi

1.35 FL OZ (40 mL)